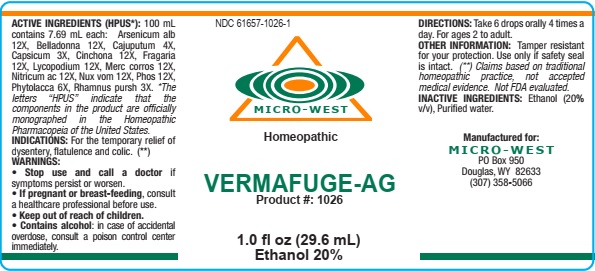 DRUG LABEL: Vermafuge -AG

NDC: 61657-1026 | Form: LIQUID
Manufacturer: White Manufacturing Inc. DBA Micro-West
Category: homeopathic | Type: HUMAN OTC DRUG LABEL
Date: 20210121

ACTIVE INGREDIENTS: STRYCHNOS NUX-VOMICA SEED 12 [hp_X]/30 mL; ARSENIC TRIOXIDE 12 [hp_X]/30 mL; CINCHONA OFFICINALIS BARK 12 [hp_X]/30 mL; CAPSICUM 3 [hp_X]/30 mL; NITRIC ACID 12 [hp_X]/30 mL; MERCURIC CHLORIDE 12 [hp_X]/30 mL; ATROPA BELLADONNA 12 [hp_X]/30 mL; CAJUPUT OIL 4 [hp_X]/30 mL; LYCOPODIUM CLAVATUM SPORE 12 [hp_X]/30 mL; PHOSPHORUS 12 [hp_X]/30 mL; PHYTOLACCA AMERICANA ROOT 6 [hp_X]/30 mL; FRANGULA PURSHIANA BARK 3 [hp_X]/30 mL; ALPINE STRAWBERRY 12 [hp_X]/30 mL
INACTIVE INGREDIENTS: ALCOHOL

DRUG FACTS

ACTIVE INGREDIENTS

Arsenicum alb 12X

Belladonna 12X

Cajuputum 4X

Capsicum 3X

Cinchona 12X

Fragaria 12X

Lycopodium 12X

Merc corros 12X

Nitricum ac 12X

Nux vom 12X

Phos 12X

Phytolacca 6X

Rhamnus pursh 3X

PURPOSE

FOR THE TEMPORARY RELIEF OF DYSENTERY, FLATULENCE, AND COLIC

KEEP OUT OF REACH OF CHILDREN

WARNING

WARNINGS: STOP USE AND CALL A DOCTOR if symptoms persist or worsen. IF PREGNANT OR BREAST FEEDING, consult a healthcare professional before use. CONTAINS ALCOHOL: in case of accidental overdose, consult a poison control center immediately.

OTHER SAFETY INFORMATION

OTHER INFORMATION: Tamper resistant for your protection. Use only if safety seal is intact.

DIRECTIONS

DIRECTIONS: Take 6 drops orally, 4 times a day. For ages 2 to adult

INDICATIONS

INDICATIONS: FOR THE TEMPORARY RELIEF OF DYSENTARY, FLATULENCE, AND COLIC

INACTIVE INGREDIENT

Alcohol 20% v/v

Purified water

MANUFACTURE

MANUFACTURED FOR

MICRO-WEST

P.O. BOX 950

DOUGLAS, WY 82633

1-307-358-5066

LABEL

NDC 61657-1026-1

MICRO-WEST

Homeopathic

VERMAFUGE-AG

Product #: 1026

1.0 fl oz (29.6 mL)

Ethanol 20%